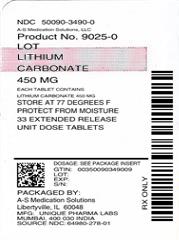 DRUG LABEL: Lithium Carbonate
NDC: 50090-3490 | Form: TABLET, EXTENDED RELEASE
Manufacturer: A-S Medication Solutions
Category: prescription | Type: Human Prescription Drug Label
Date: 20180622

ACTIVE INGREDIENTS: LITHIUM CARBONATE 450 mg/1 1
INACTIVE INGREDIENTS: SODIUM ALGINATE; SODIUM STARCH GLYCOLATE TYPE A POTATO; FERRIC OXIDE YELLOW; MAGNESIUM STEARATE; POVIDONE, UNSPECIFIED

Lithium Carbonate Extended-Release Tablets USP, 450 mg
Rx only

WARNING

Lithium toxicity is closely related to serum lithium levels, and can occur at doses close to therapeutic levels. Facilities for prompt and accurate serum lithium determinations should be available before initiating therapy (see DOSAGE AND ADMINISTRATION).

DESCRIPTION

Lithium Carbonate Extended-release Tablets USP contain lithium carbonate USP, a white granular powder with molecular formula Li2 CO3 and molecular weight 73.89. Lithium is an element of the alkali-metal group with atomic number 3, atomic weight 6.94, and an emission line at 671 nm on the flame photometer.

Lithium Carbonate Extended-release Tablets USP are available for oral administration containing 450 mg of lithium carbonate USP. Each tablet contains the following inactive ingredients: sodium alginate, sodium starch glycolate, povidone, ferric oxide yellow, magnesium stearate.

Lithium Carbonate Extended-release Tablets USP, 450 mg are designed to release a portion of the dose initially and the remainder gradually; the release pattern of the controlled release tablets reduces the variability in lithium blood levels seen with immediate release dosage forms.

The tablets comply with USP Release Test #2.

CLINICAL PHARMACOLOGY

Preclinical studies have shown that lithium alters sodium transport in nerve and muscle cells and effects a shift toward intraneuronal metabolism of catecholamines, but the specific biochemical mechanism of lithium action in mania is unknown.

INDICATIONS AND USAGE

Lithium carbonate is indicated in the treatment of manic episodes of maniac-depressive illness. Maintenance therapy revents or diminishes the intensity of subsequent episodes in those maniac-depressive patients with a history of mania.

Typical symptoms of mania include pressure of speech, motor hyperactivity, reduced need for sleep, flight of ideas, grandiosity, elation, poor judgment, aggressiveness, and possibly hostility. When given to a patient experiencing a manic episode, lithium carbonate may produce a normalization of symptomatology within 1 to 3 weeks.

WARNINGS

Lithium Toxicity

Lithium toxicity is closely related to serum lithium levels and can occur at doses close to therapeutic concentrations (see DOSAGE AND ADMINISTRATION).
Outpatients and their families should be warned that the patient must discontinue lithium therapy and contact his physician if such clinical signs of lithium toxicity as diarrhea, vomiting, tremor, mild ataxia, drowsiness, or muscular weakness occur.

Lithium carbonate may impair mental and/or physical abilities. Caution patiens about activities required alertness (e.g., operating vehicles or machinery).
Lithium should generally not be given to patients with significant renal or cardiovascular disease, severe debilitation or dehydration, or sodium depletion, since the risk of lithium toxicity is very high in such patients. If the psychiatric indication is life-threatening, and if such patients fails to respond to other measeures, lithium treatment may be undertaken with extreme caution, including daily serum lithium determinations and adjustmen to the usually low doses ordinarily tolerated by these individuals. In such instances, hospitalization is a necessity.
Unmasking of Brugada Syndrome
There have been postmarketing reports of a possible association between treatment with lithium and the unmasking of Brugada Syndrome. Brugada Syndrome is a disorder characterized by abnormal electrocardiographic (ECG) findings and a risk of sudden death. Lithium should generally be avoided in patients with Brugada Syndrome or those suspected of having Brugada Syndrome. Consultation with a cardiologist is recommended if: (1) treatment with lithium is under consideration for patients suspected of having Brugada Syndrome or patients who have risk factors for Brugada Syndrome, e.g., unexplained syncope, a family history of Brugada Syndrome, or a family history of sudden unexplained death before the age of 45 years, (2) patients who develop unexplained syncope or palpitations after starting lithium therapy.
Renal Effects
Chronic lithium therapy may be associated with diminution of renal concentrating ability, occasionally presenting as nephrogenic diabetes insipidus, with polyuria and polydipsia. Such patients should be carefully managed to avoid dehydration with resulting lithium retention and toxicity. This condition is usually reversible when lithium is discontinued.

Morphologic changes with glomerular and interstitial fibrosis and nephron atrophy have been reported in patients on chronic lithium therapy. Morphologic changes have also been seen in manic-depressive patients never exposed to lithium. The relationship between renal functional and morphologic changes and their association with lithium therapy have not been established.
When Kidney function is assessed, for baseline data prior to starting lithium therapy or thereafter, routine urinalysis and other tests may be used to evaluate tubular function (e.g., urine specific gravity or osmolality following a period of water deprivation, or 24-hour urine volume) and glomerular function (e.g., serum creatinine, creatinine clearance or proteinuria). During lithium therapy, progressive or sudden changes in renal function, even within the normal range, indicate the need for re-evaluation of treatment.
Encephalopathic Syndrome
An encephalopathic syndrome (characterized by weakness, lethargy, fever, tremulousness and confusion, extrapyramidal symptoms, leukocytosis, elevated serum enzymes, BUN, and FBS) has occurred in a few patients treated with lithium plus a neuroleptic. In some instances, the syndrome was followed by irreversible brain damage. Because of possible causal relationship between these events and the concomitant administration of lithium and neuroleptics, patients receiving such combined therapy should be monitored closely for early evidence of neurologic toxicity and treatment discontinued promptly if such signs appear. This encephalopathic syndrome may be similar to or the same as Neuroleptic Malignant Syndrome (NMS).
Concomitant Use with Neuromuscular Blocking Agents
Lithium may prolong the effects of neuromuscular blocking agents. Therefore, neuromuscular blocking agents should be given with caution to patients receiving lithium.
Usage in Pregnancy
Adverse effects on nidation in rats, embryo viability in mice, and metabolism in vitro of rat testis and human spermatozoa have been attributed to lithium, as have teratogenicity in submammalian species and cleft palates in mice.
In humans, lithium carbonate may cause fetal harm when administered to a pregnant woman. Data from lithium birth registries suggest an increase in cardiac and other anomalies, especially Ebstein’s anomaly. If this drug is used in women of childbearing potential, or during pregnancy, or if a patient becomes pregnant while taking this drug, the patient should be apprised of the potential hazard to the fetus.
Usage in Nursing Mothers
Lithium is excreted in human milk. Nursing should not be undertaken during lithium therapy except in rare and unusual circumstances where, in the view of the physician, the potential benefits to the mother outweigh possible hazard to the child.
Usage in Pediatric Patients
Since information regarding the safety and effectiveness of the lithium carbonate in children under 12 years of age is not availabel, its use in such patients is not recommended.
There has been a report of transient syndrome of acute dystonia and hyperreflexia occurring in a 15 kg pediatric patient who ingested 300 mg of lithium carbonate.

Usage in the Elderly

Elderly patients often require lower lithium dosages to acheive therapeutic serum levels. They may also exhibit adverse reactions at serum levels ordinarily tolerated by younger patients

PRECAUTIONS

General

The ability to tolerate lithium is greater during the acute manic phase and decreases when manic symptoms subside (see DOSAGE AND ADMINISTRATION).

The distribution space of lithium approximates that of total body water. Lithium is primarily excreted in urine with insignificant excretion in feces. Renal excretion of lithium is proportional to its plasma concentration. The half-life of elimination of lithium is approximately 24 hours. Lithium decreases sodium reabsorption by the renal tubules which could lead to sodium depletion. Therefore, it is essential for the patient to maintain a normal diet, including salt, and an adequate fluid intake (2500 to 3500 mL) at least during the initial stabilization period. Decreased tolerance to lithium has been reported to ensue from protracted sweating or diarrhea and, if such occur, supplemental fluid and salt should be administered under careful medical supervision and lithium intake reduced or suspended until the condition is resolved.
In addition to sweating and diarrhea, concomitant infection with elevated temperatures may also necessitate a temporary reduction or cessation of medication.
Previously existing underlying thyroid disorders do not necessarily constitute a contraindication to lithium treatment; where hypothyroidism preexists, careful monitoring of thyroid function during lithium stabilization and maintenance allows for correction of changing thyroid parameters, if any; where hypothyroidism occurs during lithium stabilization and maintenance, supplemental thyroid treatment may be used.

Information for Patients

A condition known as Brugada Syndrome may pre-exist and be unmasked by lithium therapy. Brugada Syndrome is a heart disorder characterized by abnormal electrocardiographic (ECG) findings and risk sudden death. Patients should be advised to seek immediate emmergency assistance if they experience fainting, lightheadedness, abnormal heart beats, or shortness of breath.

Drug Interactions

Caution should be used when lithium and diuretics are used concomitantly because diuretic-induced sodium loss may reduce the renal clearance of lithium and increase serum lithium levels with risk of lithium toxicity. Patients receiving such combined therapy should have serum lithium levels monitored and the lithium dosage adjusted if necessary.

Lithium levels should be closely monitored when patients initiate or discontinue NSAID use. In some cases, lithium toxicity has resulted from interactions between a NSAID and lithium. Indomethacin and piroxicam have been reported to increase significantly steady-state plasma lithium concentrations. There is also evidence that other nonsteroidal anti-inflammatory agents, including the selective cyclooxygenase-2 (COX-2) inhibitors, have the same effect. In a study conducted in healthy subjects, mean steady-state lithium plasma levels increased approximately 17% in subjects receiving lithium 450 mg BID with celecoxib 200 mg BID as compared to subjects receiving lithium alone.

Concurrent use of metronidazole with lithium may provoke lithium toxicity due to reduced renal clearance. Patients receiving such combined therapy should be monitored closely.

There is evidence that angiotensin-converting enzyme inhibitors, such as enalapril and captopril, and angiotensin II receptor antagonists, such as losartan, may substantially increase steady-state plasma lithium levels, sometimes resulting in lithium toxicity. When such combinations are used, lithium dosage may need to be decreased, and plasma lithium levels should be measured more often.

Concurrent use of calcium channel blocking agents with lithium may increase the risk of neurotoxicity in the form of ataxia, tremors, nausea, vomiting, diarrhea, and/or tinnitus. Caution is recommended.

The concomitant administration of lithium with selective serotonin reuptake inhibitors should be undertaken with caution as this combination has been reported to result in symptoms such as diarrhea, confusion, tremor, dizziness and agitation.

The following drugs can lower serum lithium concentrations by increasing urinary lithium excretion: acetazolamide, urea, xanthine preparations and alkalinizing agents such as dodium bicarbonate.

The following have also been shown to interact with lithium: methyldopa, phenytoin and carbamazapine.

ADVERSE REACTIONS

The occurrence and severity of adverse reactions are generally directly related to serum lithium concentrations as well as to individual patient sensitivity to lithium, and generally occur more frequently and with greater severity at higher concentrations.

Adverse reactions may be encountered at serum lithium concentrations below 1.5 mEq/L. Mild to moderate adverse reactions may occur at levels from 1.5 to 2.5 mEq/L, and moderate to severe reactions may be seen at concentrations from 2 mEq/L and above.
Fine hand tremor, polyuria, and mild thirst may occur during initial therapy for the acute manic phase and may persist throughout treatment. Transient and mild nausea and general discomfort may also appear during the first few days of lithium administration.
These side effects usually subside with continued treatment or a temporary reduction or cessation of dosage. If persistent, a cessation of lithium therapy may be required.

Diarrhea, vomiting, drowsiness, muscular weakness, and lack of coordination may be early signs of lithium intoxication, and can occur at lithium levels below 2 mEq/L. At higher levels, giddiness, ataxia, blurred vision, tinnitus, and a large output of dilute urine may be seen. Serum lithium concentrations above 3 mEq/L may produce a complex clinical picture involving multiple organs and organ systems. Serum lithium concentrations should not be permitted to exceed 2 mEq/L during the acute treatment phase.
The following reactions have been reported and appear to be related to serum lithium levels, including levels within the therapeutic range:
Neuromuscular/Central Nervous System: tremor, muscle hyperirritability (fasciculations, twitching, clonic movements of whole limbs), hypertonicity, ataxia, choreoathetotic movements, hyperactive deep tendon reflex, extrapyramidal symptoms including acute dystonia, cogwheel rigidity, blackout spells, epileptiform seizures, slurred speech, dizziness, vertigo, downbeat nystagmus, incontinence of urine or feces, somnolence, psychomotor retardation, restlessness, confusion, stupor, coma, tongue movements, tics, tinnitus, hallucinations, poor memory, slowed intellectual functioning, startled response, worsening of organic brain syndromes, myasthenia gravis (rarely).
Cardiovascular: cardiac arrhythmia, hypotension, peripheral circulatory collapse, bradycardia, sinus node dysfunction with severe bradycardia (which may result in syncope), Unmasking of Brugada Syndrome (see WARNINGS: Unmasking of Brugada Syndrome and PRECAUTIONS: Information for the patients).
Gastrointestinal: anorexia, nausea, vomiting, diarrhea, gastritis, salivary gland swelling, abdominal pain, excessive salivation, flatulence, indigestion.
Genitourinary: glycosuria, decreased creatinine clearance, albuminuria, oliguria, and symptoms of nephrogenic diabetes insipidus including polyuria, thirst and polydipsia.
Dermatologic: drying and thinning of hair, alopecia, anesthesia of skin, acne, chronic folliculitis, xerosis cutis, psoriasis or its exacerbation, generalized pruritus with or without rash, cutaneous ulcers, angioedema.
Autonomic: blurred vision, dry mouth, impotence/sexual dysfunction.
Thyroid Abnormalities: euthyroid goiter and/or hypothyroidism (including myxedema) accompanied by lower T3 and T4. ^131I uptake may be elevated (see PRECAUTIONS). Paradoxically, rare cases of hyperthyroidism have been reported.
EEG Changes: diffuse slowing, widening of frequency spectrum, potentiation and disorganization of background rhythm.
EKG Changes:reversible flattening, isoelectricity or inversion of T-waves.
Miscellaneous: fatigue, lethargy, transient scotomata, exophthalmos, dehydration, weight loss, leukocytosis, headache, transient hyperglycemia, hypercalcemia, hyperparathyroidism, excessive weight gain, edematous swelling of ankles or wrists, metallic taste, dysgeusia/taste distortion, salty taste, thirst, swollen lips, tightness in chest, swollen and/or painful joints, fever, polyarthralgia, and dental caries.
Some reports of nephrogenic diabetes insipidus, hyperparathyroidism, and hypothyroidism which persist after lithium discontinuation have been received.
A few reports have been received of the development of painful discoloration of fingers and toes and coldness of the extremities within one day of starting of treatment with lithium. The mechanism through which these symptoms (resembling Raynaud’s Syndrome) developed is not known. Recovery followed discontinuance.

Cases of pseudotumor cerebri (increased intracranial pressure and papilledema) may have been reported with lithium use. If undected, this condition may result in enlargement of the blind spot, constriction of visula fields and eventual blindness due to optic atrophy. Lithium should be discontinued, if clinically possible, if this syndrome occurs.

OVERDOSAGE

The toxic concentrations for lithium are close to the therapeutic levels. It is therefore important that patients and their families be cautioned to watch for early toxic symptoms and to discontinue the drug and inform the physician should they occur. (Toxic symptoms are listed in detail under ADVERSE REACTIONS).

Treatment

No specific antidote for lithium poisoning is known. Early symptoms of lithium toxicity can usually be treated by reduction or cessation of dosage of the drug and resumption of the treatment at a lower dose after 24 to 48 hours. In severe cases of lithium poisoning, the first and foremost goal of treatment consists of elimination of this ion from the patient. Treatment is essentially the same as that used in barbiturate poisoning: 1) gastric lavage, 2) correction of fluid and electrolyte imbalance and, 3) regulation of kidney functioning. Urea, mannitol, and aminophylline all produce significant increases in lithium excretion. Hemodialysis is an effective and rapid means of removing the ion from the severely toxic patient. Infection prophylaxis, regular chest X-rays, and preservation of adequate respiration are essential.

DOSAGE AND ADMINISTRATION

Doses of extended-release tablets are usually given b.i.d. (approximately 12-hour intervals). When initiating therapy with immediate-release or extended-release lithium, dosage may be individualized according to serum levels and clinical response.

When switching a patient from immediate-release capsules to the lithium carbonate extended-release tablets USP, give the same total daily dose when possible. Most patients on maintenance therapy are stabilized on 900 mg daily, e.g., lithium extended-release tablets. 450 mg, b.i.d. When the previous dosaqge of immediate-release lithium is not a multiple of 450 mg, e.g., 1500 mg, initiate lithium extended-release tablet at the multiple of 450 mg nearest to, byt below, the original daily dose, i.e., 1350 mg. When the two doses are unequal, give the larger dose in the evening. In the above example with a total daily dose of 1350 mg, generally 450 mg of lithium carbonate extended-release tablets should be given in the morning and 900 mg of lithiumcarbonate extended-release tablets in the evening. If desired, the total daily dose of 1350 mg can be given in three parts of 450 mg doses of lithium carbonate extended-release tablets. Thses patients should be monitored at 1- to 2-week intervals, and dosage adjusted if necessary, until stable and satisfactory serum levels and clinican state is acheived.

When patients require closer titration than that available with lithium carbonate extended-release tablets in increments of 450 mg, immediate-release capsules should be used.

Acute Mania

Optimal patient response can usually be established and maintained with 1800 mg/day in divided doses. Such doses will normally produce an effective serum lithium concentration ranging between 1 and 1.5 mEq/L.

Dosage must be individualized according to serum levels and clinical response. Regular monitoring of the patient’s clinical state and of serum lithium levels is necessary. Serum levels should be determined twice per week during the acute phase, and until the serum level and clinical condition of the patient have been stabilized.

Long-Term Control
Desirable serum lithium concentrations are 0.6 to 1.2 mEq/L. Dosage will vary from one individual to another, but usually 900 to 1200 mg/day generally in divided dosages will maintain this level. Serum lithium levels in uncomplicated cases receiving maintenance therapy during remission should be monitored at least every two months.

Patients abnormally sensitive to lithium may exhibit toxic signs at serum concentrations of 1 mEq/L.

N.B.

Blood samples for serum lithium determinations should be drawn immediately prior to the next dose when lithium concentrations are relatively stable (i.e., 8 to 12 hours after previous dose). Total reliance must not be placed on serum concentrations alone. Accurate patient evaluation requires both clinical and laboratory analysis.

Elderly patients often respond to reduced dosage, and may vary exhibit signs of toxicity at serum levels ordinarily tolerated by younger patients.

HOW SUPPLIED

Product: 50090-3490

NDC: 50090-3490-0 33 TABLET, EXTENDED RELEASE in a BOTTLE

Storage Conditions

Store at 25°C (77°F); excursions permitted to 15° to 30°C [See USP Controlled Room Temperature.] Protect from moisture. Dispense in tight, child-resistant container USP/NF.